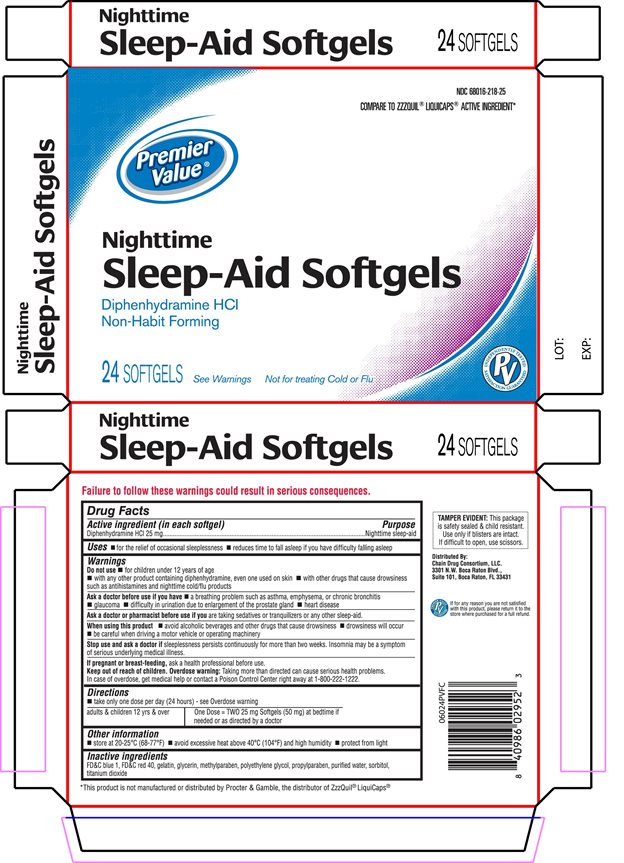 DRUG LABEL: Premier Value Nighttime Sleep Aid Softgels
NDC: 68016-218 | Form: CAPSULE, GELATIN COATED
Manufacturer: Chain Drug Consortium
Category: otc | Type: HUMAN OTC DRUG LABEL
Date: 20160615

ACTIVE INGREDIENTS: Diphenhydramine Hydrochloride 50 mg/2 1
INACTIVE INGREDIENTS: FD&C Blue No. 1; FD&C Red No. 40; gelatin; glycerin; METHYLPARABEN; polyethylene glycols; PROPYLPARABEN; water; sorbitol; titanium dioxide

PREMIER VALUE SLEEP-AID SOFTGELS

Drug Facts

Active ingredients (in each softgel)

Diphenhydramine HCl 25 mg

Purpose

nighttime sleep-aid

Uses

- for the relief of occasional sleeplessness
- reduces time to fall asleep if you have difficulty falling asleep

Warnings

Do not use

- for children under 12 years of age
- with any other product containing diphenhydramine, even one used on skin.
- with other drugs that cause drowsiness such as antihistamines and nighttime cold/flu products

Ask a doctor before use if you have

- a breathing problem such as asthma, emphysema, or chronic bronchitis
- glaucoma
- difficulty in urination due to enlargement of the prostate gland
- heart disease

Ask a doctor or pharmacist before use if you are taking sedatives or tranquilizers or any other sleep aid

When using this product

- avoid alcoholic beverages and other drugs that cause drowsiness
- drowsiness will occur
- be careful when driving a motor vehicle or operating machinery

Stop use and ask a doctor if sleeplessness persists continuously for more than 2 weeks. Insomnia may be a symptom of serious underlying medical illness.

PREGNANCY OR BREAST FEEDING

If pregnant or breast-feeding, ask a health professional before use.

Keep out of reach of children. Overdose warning: Taking more than directed can cause serious health problems. In case of overdose, get medical help or contact a Poison Control Center right away.

Directions

- take only one dose per day (24 hours) - see Overdose warning

adults & children
12 yrs & over

One dose = TWO 25 mg Softgels (50 mg)
at bed time if needed or as directed by a doctor

Other information

- store at 20-25° C (68-77° F)
- avoid excessive heat above 40° C (104° F) and high humidity
- protect from light

Inactive ingredients

FD&C blue 1, FD&C red 40, gelatin, glycerin, methylparaben, polyethylene glycol, propylparaben, purified water, sorbitol, titanium dioxide

Failure to follow these warnings could result in serious consequences

TAMPER EVIDENT: This package is safety sealed & child resistant. Use only if blisters are intact. If difficult to open, use scissors.

Distributed by:

Chain Drug Consortium LLC.

3301 N.W. Boca Raton Blvd.

Suite 101, Boca Raton FL 33431

*This product is not manufactured or distributed by Procter & Gamble, the distributor of ZzzQuil® Liquicaps.

PRINCIPAL DISPLAY PANEL

Premier Value
Nighttime

Sleep-Aid Softgels
Diphenhydramine HCl

Non Habit Forming

Not for treating Cold or Flu

See Warnings

Compare to ZzzQuil® Liquicaps® active ingredient*

24 SOFTGELS